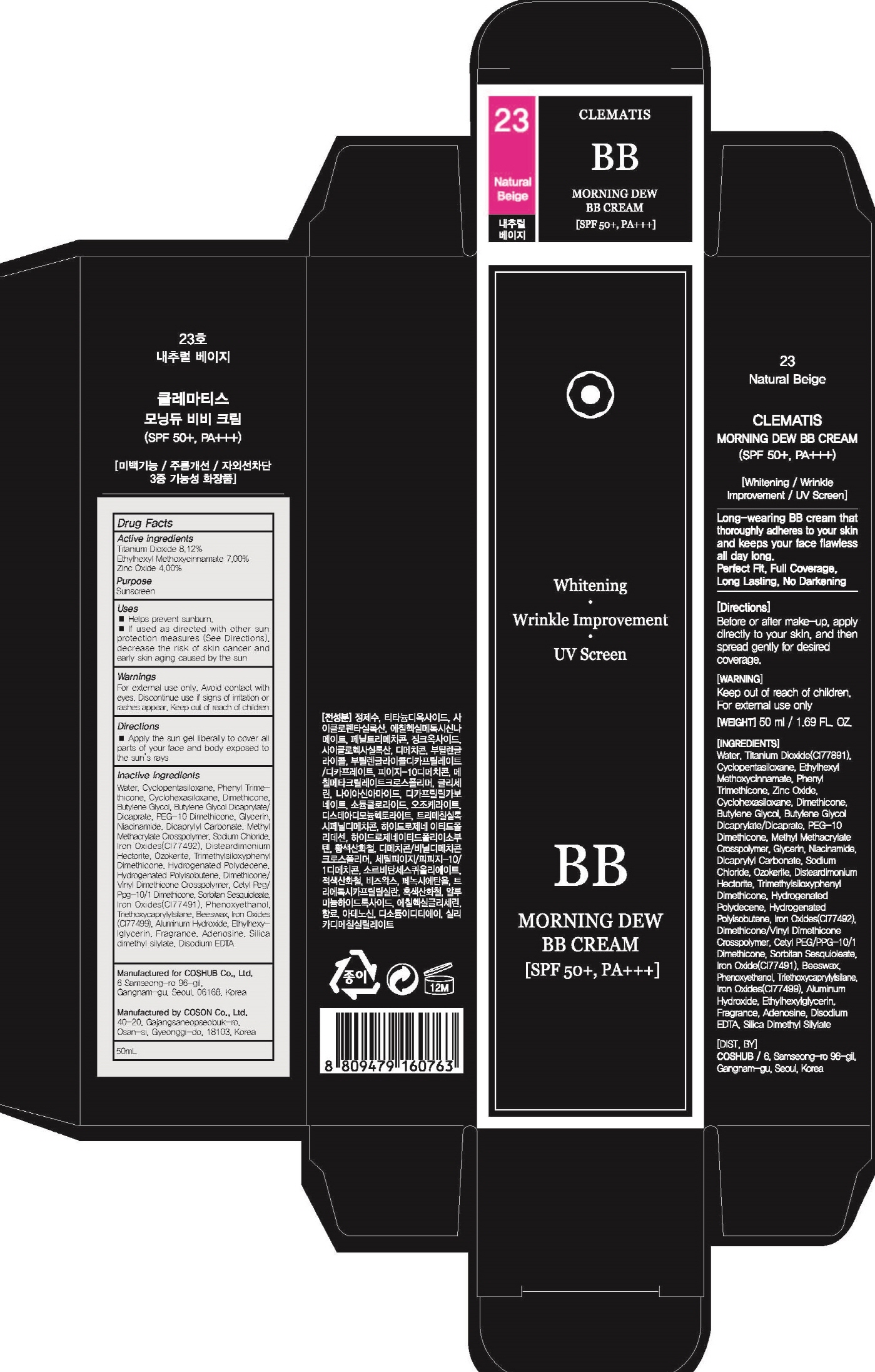 DRUG LABEL: CLEMATIS Morning dew BB 23 Natural Beige
NDC: 71702-100 | Form: CREAM
Manufacturer: Coshub Co., Ltd.
Category: otc | Type: HUMAN OTC DRUG LABEL
Date: 20170905

ACTIVE INGREDIENTS: Titanium Dioxide 4.06 g/50 mL; Octinoxate 3.50 g/50 mL; Zinc Oxide 2.00 g/50 mL
INACTIVE INGREDIENTS: Water; Phenyl Trimethicone

ACTIVE INGREDIENT

Active ingredients: Titanium Dioxide 8.12%, Ethylhexyl Methoxycinnamate 7.00%, Zinc Oxide 4.00%

INACTIVE INGREDIENT

Inactive ingredients: Water, Cyclopentasiloxane, Phenyl Trimethicone, Cyclohexasiloxane, Dimethicone, Butylene Glycol, Butylene Glycol Dicaprylate/Dicaprate, PEG-10 Dimethicone, Glycerin, Niacinamide, Dicaprylyl Carbonate, Methyl Methacrylate Crosspolymer, Sodium Chloride, Iron Oxides(CI77492), Disteardimonium Hectorite, Ozokerite, Trimethylsiloxyphenyl Dimethicone, Hydrogenated Polydecene, Hydrogenated Polyisobutene, Dimethicone/Vinyl Dimethicone Crosspolymer, Cetyl Peg/Ppg-10/1 Dimethicone, Sorbitan Sesquioleate, Iron Oxides(CI77491), Phenoxyethanol, Triethoxycaprylylsilane, Beeswax, Iron Oxides(CI77499), Aluminum Hydroxide, Ethylhexylglycerin, Fragrance, Adenosine, Silica dimethyl silylate, Disodium EDTA

PURPOSE

Purpose: Sunscreen

WARNINGS

Warnings: For external use only. Avoid contact with eyes. Replace the cap after use. Discontinue use if signs of irritation or rashes appear. Keep out of reach of children.

DESCRIPTION

Uses: - Helps prevent sunburn. - If used as directed with other sun protection measures (See Directions), decrease the risk of skin cancer and early skin aging caused by the sun

Directions: Apply the sun gel liberally to cover all parts of your face and body exposed to the sun's rays.